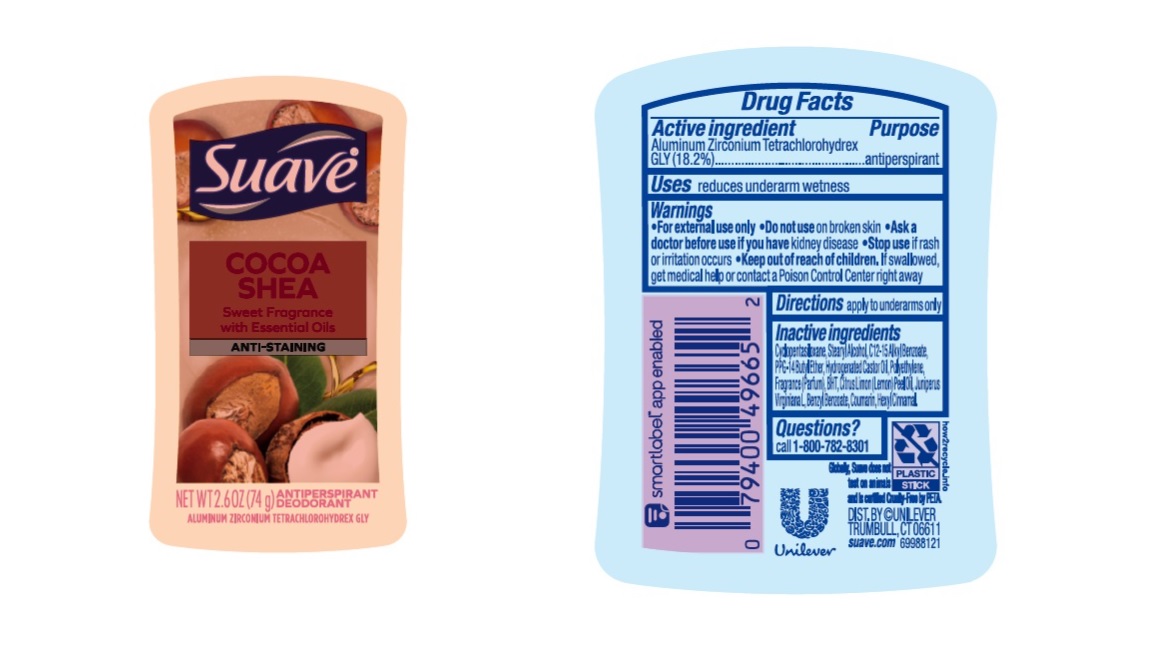 DRUG LABEL: Suave
NDC: 64942-2146 | Form: STICK
Manufacturer: Conopco Inc. d/b/a/ Unilever
Category: otc | Type: HUMAN OTC DRUG LABEL
Date: 20230821

ACTIVE INGREDIENTS: ALUMINUM ZIRCONIUM TETRACHLOROHYDREX GLY 18.2 g/100 g
INACTIVE INGREDIENTS: HIGH DENSITY POLYETHYLENE; ALKYL (C12-15) BENZOATE; HYDROGENATED CASTOR OIL; PPG-14 BUTYL ETHER; CYCLOMETHICONE 5; BUTYLATED HYDROXYTOLUENE; STEARYL ALCOHOL; BENZYL BENZOATE; .ALPHA.-HEXYLCINNAMALDEHYDE; COUMARIN

Suave Cocoa Shea Anti-Staining Antiperspirant Deodorant

Drug Facts

Active ingredient

Aluminum Zirconium Tetrachlorohydrex GLY (18.2 %)

Purpose

antiperspirant

Uses

reduces underarm wetness

Warnings

• For externaluse only.
• Do not use on broken skin .
• Ask a doctor before use if you have kidney disease.
• Stop use if rash or irritation occurs.

• Keep out of reach of children.

If swallowed, get medical help or contact a Poison Control Center right away.

Directions

apply to underarms only

Inactive ingredients

Cyclopentasiloxane, Stearyl Alcohol, C12-15 Alkyl Benzoate, PPG-14 Butyl Ether, Hydrogenated Castor Oil, Fragrance (Parfum), Polyethylene, BHT, Citrus Aurantium Dulcis Peel Oil, Juniperus Virginala L, Benzyl Benzoate, Coumarin, Hexyl Cinnamal.

Questions?

Call 1-800-782-8301